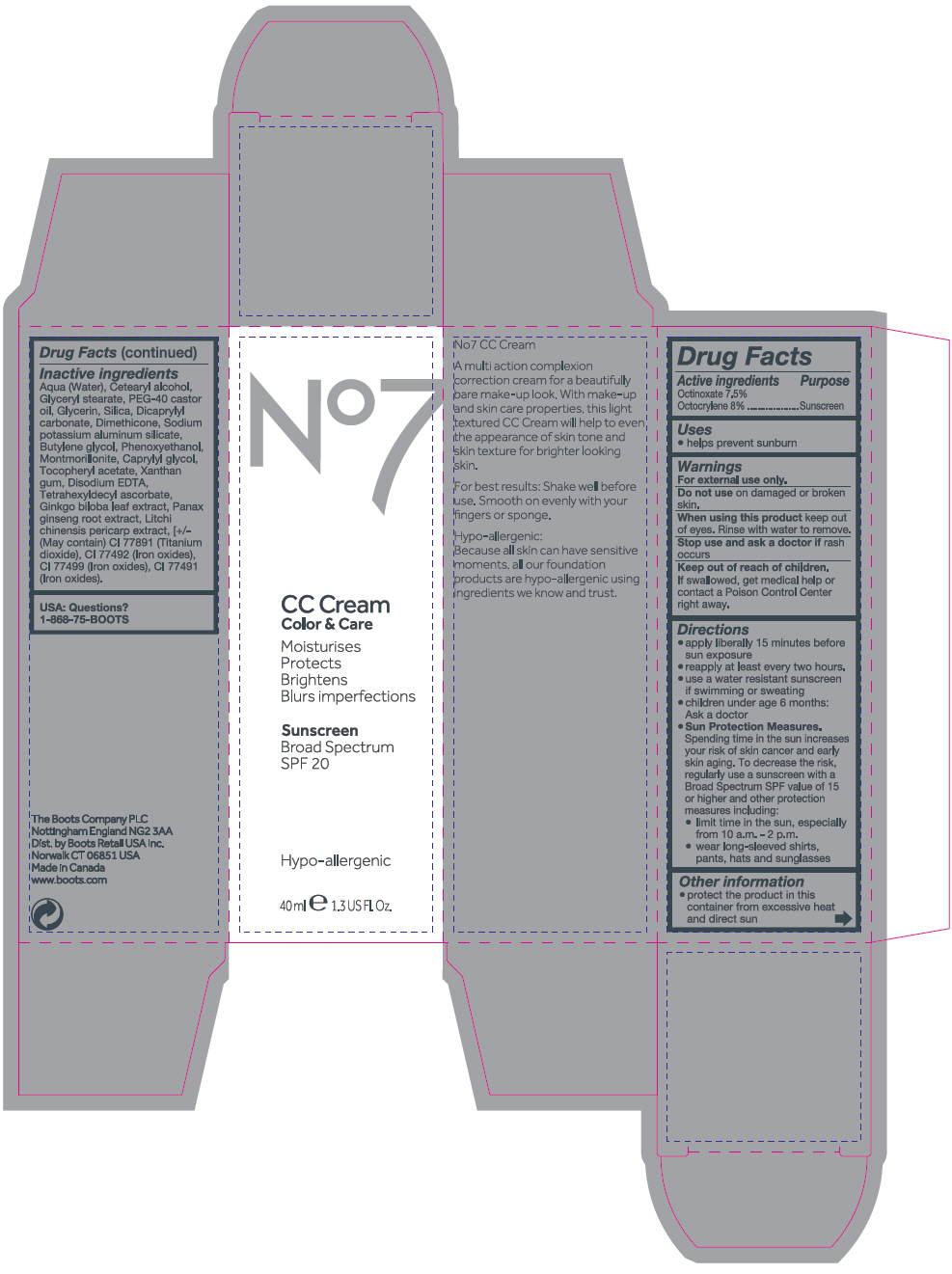 DRUG LABEL: No7 CC 
NDC: 66559-2977 | Form: EMULSION
Manufacturer: Cosmetica Laboratories Inc.
Category: otc | Type: HUMAN OTC DRUG LABEL
Date: 20140402

ACTIVE INGREDIENTS: Octocrylene 80 mg/1 mL; Octinoxate 75 mg/1 mL
INACTIVE INGREDIENTS: CETOSTEARYL ALCOHOL; GLYCERYL MONOSTEARATE; PEG-40 CASTOR OIL; GLYCERIN; SILICON DIOXIDE; DICAPRYLYL CARBONATE; DIMETHICONE; BUTYLENE GLYCOL; MONTMORILLONITE; .ALPHA.-TOCOPHEROL ACETATE; XANTHAN GUM; EDETATE DISODIUM; TETRAHEXYLDECYL ASCORBATE; GINKGO; ASIAN GINSENG; LITCHI FRUIT; CAPRYLYL GLYCOL; PHENOXYETHANOL; TITANIUM DIOXIDE; FERRIC OXIDE RED; FERRIC OXIDE YELLOW; FERROSOFERRIC OXIDE; WATER

No7 CC Cream

Drug Facts

Active ingredients

Octinoxate 7.5%
Octocrylene 8%

Purpose

Sunscreen

Uses

- helps prevent sunburn

Warnings

For external use only.

Do not use on damaged or broken skin.

When using this product keep out of eyes. Rinse with water to remove.

Stop use and ask a doctor if rash occurs

Keep out of reach of children. If swallowed, get medical help or contact a Poison Control Center right away.

Directions

- apply liberally 15 minutes before sun exposure
- reapply at least every two hours.
- use a water resistant sunscreen if swimming or sweating
- children under age 6 months: Ask a doctor
- Sun Protection Measures. Spending time in the sun increases your risk of skin cancer and early skin aging. To decrease the risk, regularly use a sunscreen with a Broad Spectrum SPF value of 15 or higher and other protection measures including:
  - limit time in the sun, especially from 10 a.m. - 2 p.m.
  - wear long-sleeved shirts, pants, hats and sunglasses

Other information

- protect the product in this container from excessive heat and direct sun

Inactive ingredients

Aqua (Water), Cetearyl alcohol, Glyceryl stearate, PEG-40 castor oil, Glycerin, Silica, Dicaprylyl carbonate, Dimethicone, Sodium potassium aluminum silicate, Butylene glycol, Phenoxyethanol, Montmorillonite, Caprylyl glycol, Tocopheryl acetate, Xanthan gum, Disodium EDTA, Tetrahexyldecyl ascorbate, Ginkgo biloba leaf extract, Panax ginseng root extract, Litchi chinensis pericarp extract, [+/- (May contain) CI 77891 (Titanium dioxide), CI 77492 (Iron oxides), CI 77499 (Iron oxides), CI 77491 (Iron oxides).

USA: Questions?

1-868-75-BOOTS

Dist. by Boots Retail USA Inc.
Norwalk CT 06851 USA

PRINCIPAL DISPLAY PANEL - 40 ml Tube Carton - Light

No7

CC Cream
Color & Care

Moisturises
Protects
Brightens
Blurs imperfections

Sunscreen
Broad Spectrum
SPF 20

Hypo-allergenic

40 ml e 1.3 US Fl. Oz.

PRINCIPAL DISPLAY PANEL - 40 ml Tube Carton - Medium

No7

CC Cream
Color & Care

Moisturises
Protects
Brightens
Blurs imperfections

Sunscreen
Broad Spectrum
SPF 20

Hypo-allergenic

40 ml e 1.3 US Fl. Oz.